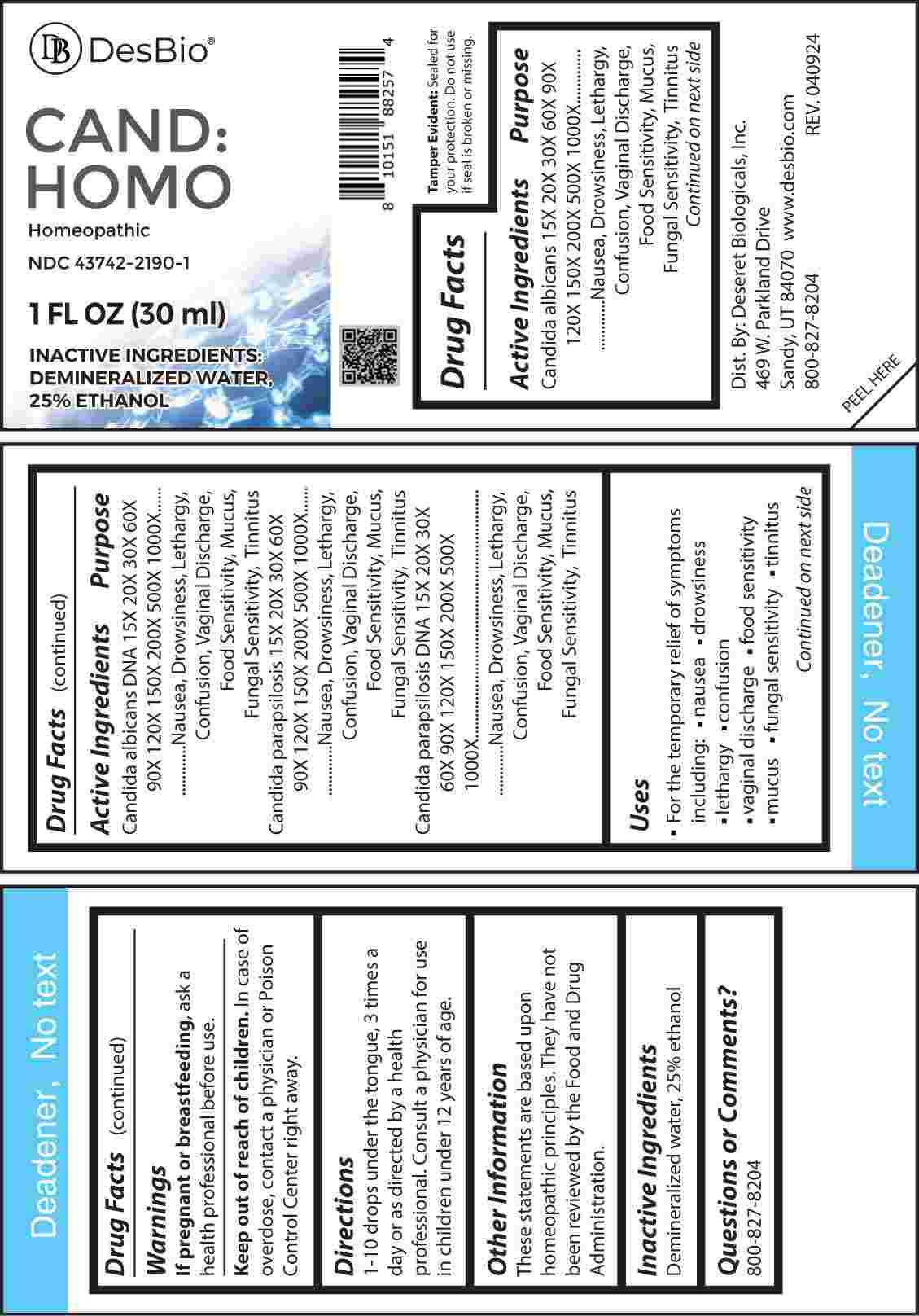 DRUG LABEL: CAND HOMO
NDC: 43742-2190 | Form: LIQUID
Manufacturer: Deseret Biologicals, Inc.
Category: homeopathic | Type: HUMAN OTC DRUG LABEL
Date: 20240802

ACTIVE INGREDIENTS: CANDIDA ALBICANS 15 [hp_X]/1 mL; CANDIDA ALBICANS DNA 15 [hp_X]/1 mL; CANDIDA PARAPSILOSIS 15 [hp_X]/1 mL; CANDIDA PARAPSILOSIS DNA 15 [hp_X]/1 mL
INACTIVE INGREDIENTS: WATER; ALCOHOL

DRUG FACTS:

ACTIVE INGREDIENTS:

Candida Albicans 15X, 20X, 30X, 60X, 90X, 120X, 150X, 200X, 500X, 1000X, Candida Albicans DNA 15X, 20X, 30X, 60X, 90X, 120X, 150X, 200X, 500X, 1000X, Candida Parapsilosis 15X, 20X, 30X, 60X, 90X, 120X, 150X, 200X, 500X, 1000X, Candida Parapsilosis DNA 15X, 20X, 30X, 60X, 90X, 120X, 150X, 200X, 500X, 1000X.

PURPOSES:

Candida Albicans – Nausea, Drowsiness, Lethargy, Confusion, Vaginal Discharge, Food Sensitivity, Mucus, Fungal Sensitivity, Tinnitus, Candida Albicans DNA - Nausea, Drowsiness, Lethargy, Confusion, Vaginal Discharge, Food Sensitivity, Mucus, Fungal Sensitivity, Tinnitus, Candida Parapsilosis - Nausea, Drowsiness, Lethargy, Confusion, Vaginal Discharge, Food Sensitivity, Mucus, Fungal Sensitivity, Tinnitus, Candida Parapsilosis DNA - Nausea, Drowsiness, Lethargy, Confusion, Vaginal Discharge, Food Sensitivity, Mucus, Fungal Sensitivity, Tinnitus

USES:

• For the temporary relief of symptoms including:

• nausea • drowsiness • lethargy • confusion

• vaginal discharge • food sensitivity • mucous

• fungal sensitivity • tinnitus

These statements are based upon homeopathic principles. They have not been reviewed by the Food and Drug Administration.

WARNINGS:

If pregnant or breast-feeding, ask a health professional before use.

Keep out of reach of children. In case of overdose, contact a physician or Poison Control Center right away.

Tamper Evident: Sealed for your protection. Do not use if seal is broken or missing.

KEEP OUT OF REACH OF CHILDREN:

In case of overdose, contact a physician or Poison Control Center right away.

DIRECTIONS:

1-10 drops under the tongue, 3 times a day or as directed by a health professional. Consult a physician for use in children under 12 years of age.

INACTIVE INGREDIENTS:

Demineralized water, 25% ethanol

QUESTIONS:

Dist. By: Deseret Biologicals, Inc.
469 W. Parkland Drive
Sandy, UT 84070

www.desbio.com

800-827-8204

PACKAGE LABEL DISPLAY:

DesBio

CAND:HOMO

Homeopathic

NDC 43742-2190-1

1 FL OZ (30ml)